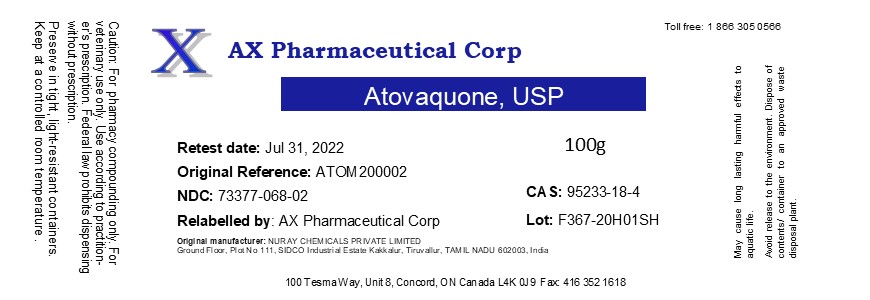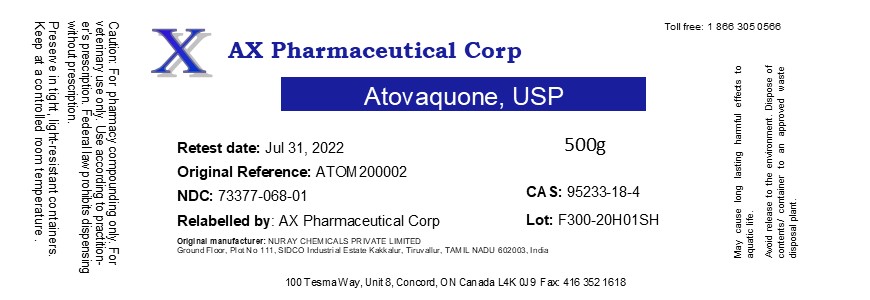 DRUG LABEL: Atovaquone
NDC: 73377-068 | Form: POWDER
Manufacturer: AX Pharmaceutical Corp
Category: other | Type: BULK INGREDIENT
Date: 20200910

ACTIVE INGREDIENTS: ATOVAQUONE 1 g/1 g

Atovaquone